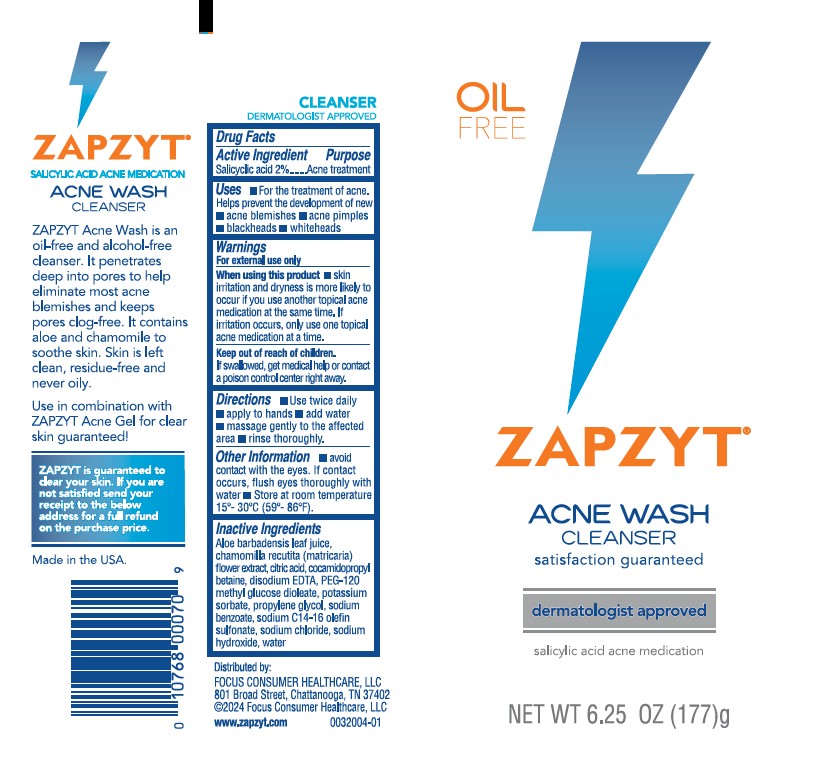 DRUG LABEL: Zapzyt Acne Wash Cleanser
NDC: 71687-0007 | Form: GEL
Manufacturer: Focus Consumer Healthcare, LLC
Category: otc | Type: HUMAN OTC DRUG LABEL
Date: 20260116

ACTIVE INGREDIENTS: SALICYLIC ACID 2 g/100 g
INACTIVE INGREDIENTS: PROPYLENE GLYCOL; ALOE BARBADENSIS LEAF JUICE; SODIUM C14-16 OLEFIN SULFONATE; EDETATE DISODIUM; CHAMOMILE FLOWER OIL; COCAMIDOPROPYL BETAINE; PEG-120 METHYL GLUCOSE DIOLEATE; WATER; SODIUM CHLORIDE; SODIUM HYDROXIDE; SODIUM BENZOATE; POTASSIUM SORBATE; ANHYDROUS CITRIC ACID

Zapzyt Acne Wash Cleanser

Active ingredient

Salicylic Acid 2%

Purpose

Acne treatment

Uses

For the treatment of acne. Helps prevent the development of new

- acne blemishes
- acne pimples
- blackheads
- whiteheads

Warnings

For external use only.

When using this product

- skin irritation and dryness is more likely to occur if you use another topical acne medication at the same time. If irritation occurs, use only one topical acne medication at a time.

Keep out of reach of children. If swallowed, get medical help or contact a poison control center right away.

Directions

- Use twice daily
- apply to hands
- add water
- massage gently to the affected area
- rinse thoroughly.

Other information

- avoid contact with the eyes. If contact occurs, flush eyes thoroughly with water.
- Store at room temperature 15o - 30oC (59o - 86oF).

Inactive ingredients

Aloe barbadensis leaf juice, chamomilla recutita (matricaria) flower sxtract, citric acid, cocamidopropyl betaine, disodium EDTA, PEG-120 methyl glucose dioleate, potassium sorbate, propylene glycol, sodium benzoate, sodium C14-16 olefin sulfonate, sodium chloride, sodium hydroxide, water